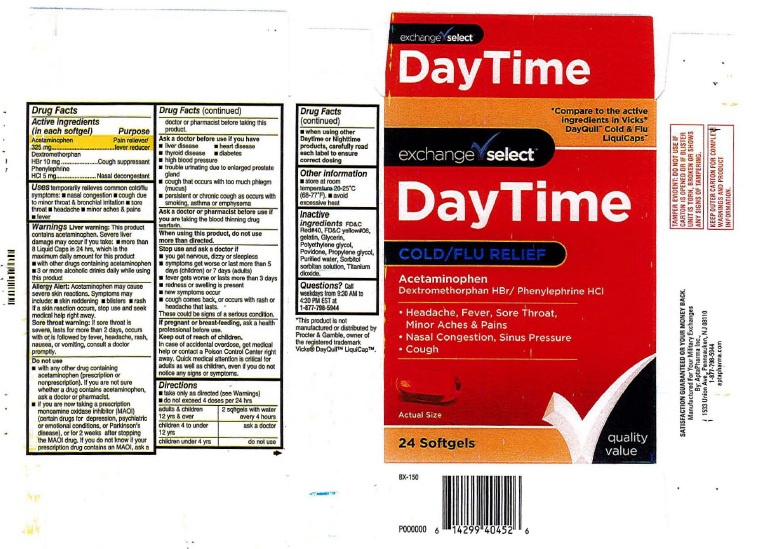 DRUG LABEL: DayTime Cold/Flu Relief
NDC: 55301-604 | Form: CAPSULE, LIQUID FILLED
Manufacturer: ARMY AND AIR FORCE EXCHANGE SERVICE
Category: otc | Type: HUMAN OTC DRUG LABEL
Date: 20251219

ACTIVE INGREDIENTS: ACETAMINOPHEN 325 mg/1 1; DEXTROMETHORPHAN HYDROBROMIDE 10 mg/1 1; PHENYLEPHRINE HYDROCHLORIDE 5 mg/1 1
INACTIVE INGREDIENTS: FD&C RED NO. 40; FD&C YELLOW NO. 6; GELATIN; GLYCERIN; POLYETHYLENE GLYCOL, UNSPECIFIED; POVIDONE; PROPYLENE GLYCOL; WATER; SORBITOL; SORBITAN; TITANIUM DIOXIDE

exchange select DayTime Cold/Flu Relief

Drug Facts

Active ingredients
(in each Softgel)
Acetaminophen ................325 mg

Dextromethorphan HBr ......10 mg

Phenylephrine HCl .........5 mg

Purpose

Acetaminophen ........................Pain reliever/Fever reducer

Dextromethorphan HBr .............Cough suppressant

Phenylephrine HCl ............... Antihistamine

INDICATIONS AND USAGE

Usestemporarily relieves common cold/flu
symptoms: ■ nasal congestion ■cough due to
to minor throat & bronchial irritation ■ sore
throat ■ headache ■ minor aches and pains
■ fever

WARNINGS

WarningsLiver warning : This product
contains acetaminophen. Severe liver
damage may occur if you take ■ more than
4doses in 24 hrs, which is the maximum
daily amount for this product ■ with other
drugs containing acetaminophen ■ 3 or more
alcoholic drinks daily while using this product.

Allergy Alert:Acetaminophen may cause
severe skin reactions. Symptoms may
include ■ skin reddening ■ blisters ■ rash.
If skin reaction occurs, stop use and seek
medical help right away.

Sore throat warning: If sore throat is
severe, lasts for more than 2 days, occurs
with or is followed by fever, headache, rash,
nausea or vomiting, consult a doctor
promptly.

Do not use:

■with any other products containing
Acetaminophen (prescription or
nonprescription). If you are not sure whether
a drug contains acetaminophen, ask a doctor
or pharmacist
■ if you are now taking a prescription
Monoamine oxidase inhibitor (MAOI) (certain
drugs for depression, psychiatric, or
emotional conditions, or Parkinson's
disease), or for 2 weeks after stopping the
MAOI drug. If you do not know if your
prescription drug contains an MAOI, ask
a doctor or pharmacist before taking this
product.

Ask a doctor before use if you have
■ liver disease ■ heart disease
■ thyroid disease ■ diabetis
■ high blood pressure
■ trouble urinating due to an enlarged prostate
gland
■ cough that occurs with too much phlegm
(mucus)
■ persistant or chronic cough as occurs with
smoking, asthma or emphysema

Ask a doctor or pharmacistbefore use if you are
if you are taking the blood thinning drug warfarin.

When using this product, do not use
more than directed.

Stop use and ask a doctor if
■ you get nervous, dizzy or sleepless
■ symptoms get worse or"last more than 5 days (children) or 7 days (adults)
■ fever gets worse or lasts more than 3 days
■ redness or swelling is present
■ new symptoms occur
■ cough comes back or occurs with rash or headache that lasts.
These could be signs of a serious condition

PREGNANCY OR BREAST FEEDING

If pregnant or breast-feeding, ask a health professional before use.

Keep out of reach of children.

In case of overdose, get medical help or contact a
Poison Control Center right away.

OVERDOSAGE

In case of accidental overdose, get medical
help or contact a Poison Control center right
away. Quick medical attention is critical for
adults as well as children even if you do not
notice any signs or symptoms.

DOSAGE AND ADMINISTRATION

Directions ■ take only as directed (see Warning)
■ do not exceed 4 doses per 24 hours

adults & children 12 yrs & over | 2 soft gels with water every 4 hours
children 4 to under 12 years: | ask a doctor
children under 4 years: | do not use

■ when using other
Daytime or Nighttime
products, carefully read
each label to ensure
correct dosing.

Other information
■ store at room temperature 20-25º C (68-77º F)
■ avoid excessive heat

Inactive ingredientsFD&C
Red No. 40, FD&C Yellow No.6,
gelatin, Glycerin,
Polyethylene glycol,
Povidone, propylene glycol,
Purified water, Sorbitol
sorbitan solution, Titanium
dioxide

QUESTIONS

Questions? Call Weekdays from 9:30 AM to 4:30 PM EST at
1-877-798-5944

Product Label: exchange select DayTime Cold/Flu Relief

exchange select

DayTime

COLD/FLU RELIEF

24 Softgels

Manufactured For Your Military Exchange

By AptaPharma Inc.,

1533 Union Avenue, Pennsauken, NJ 08110

1-877-798-5944

aptapharma.com

res